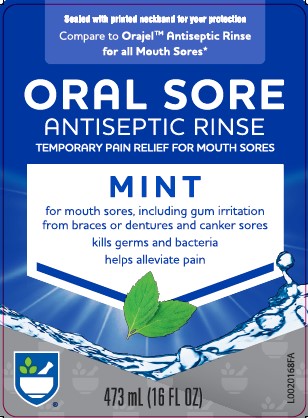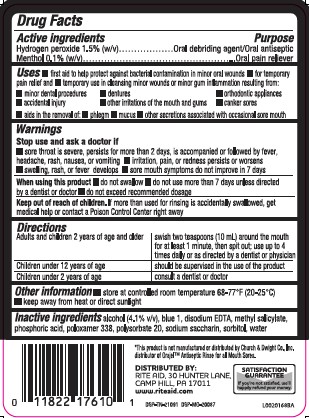 DRUG LABEL: Oral Sore Antiseptic
NDC: 11822-3024 | Form: LIQUID
Manufacturer: Rite Aid Corporation
Category: otc | Type: HUMAN OTC DRUG LABEL
Date: 20260130

ACTIVE INGREDIENTS: HYDROGEN PEROXIDE 1.5 mg/1 mL; MENTHOL 1 mg/1 mL
INACTIVE INGREDIENTS: ALCOHOL; FD&C BLUE NO. 1; EDETATE DISODIUM ANHYDROUS; METHYL SALICYLATE; PHOSPHORIC ACID; POLOXAMER 338; POLYSORBATE 20; SACCHARIN SODIUM; SORBITOL; WATER

Rite Aid 024.000/024AB
Oral Sore Antiseptic Rinse

active ingredients

Hydrogen peroxide 1.5% (w/v)

Menthol 0.1% (w/v)

purpose

Oral debriding agent/Oral antiseptic
Oral pain reliever

uses

- first aid to help protect against bacterial contamination in minor oral wounds
- for temporary pain relief and
- temporary use in cleansing minor wounds or minor gum inflammation resulting from:
- minor dental procedures
- dentures
- orthodontic appliances
- accidental injury
- other irritations of the mouth and gums
- canker sores
- aids in the removal of:
- phlegm
- mucus
- other secretions associated with occasional sore mouth

warnings

for this product

Stop use and ask a doctor if

- sore throat is severe, persists for more than 2 days, is accompanied or followed by fever, headache, rash, nausea, or vomiting
- irritation, pain, or redness persists or worsens
- swelling, rash, or fever develops
- sore mouth symptoms do not improve in 7 days

When using this product

- do not swallow
- do not use more than 7 days unless directed by a dentist or doctor
- do not exceed recommended dosage

Keep out of reach of children.

If more than used for rinsing is accidentally swallowed, get medical help or contact a Poison Control Center right away.

directions

Adults and children 2 years of age and older - swish two teaspoons (10 mL) around the mouth for at least 1 minute, then spit out; use up to 4 times daily or as directed by a dentist or physician

Children under 12 years of age - should be supervised in the use of the product

Children under 2 years of age - consult a dentist or doctor

other information

- store at controlled room temperature 68-77°F (20-25°C)
- keep away from heat or direct sunlight

inactive ingredients

alcohol (4.1% v/v), blue 1, disodium EDTA, methyl salicylate, phosphoric acid, poloxamer 338, polysorbate 20, sodium saccharin, sorbitol, water

Disclaimer

*This product is not manufactured or distributed by Church & Dwight Co., Inc. distributor of OrajelAntiseptic Rinse for all Mouth Sores.

ADVERSE REACTION

SATISFACTION GUARANTEE

If you're not satisfed, we'll happily refund your money.

DISTRIBUTED BY:

RITE AID, 30 HUNTER LANE,

CAMP HILL, PA 17011

www.riteaid.com

DSP-TN-21091 DSP-MO-20087

principal display panel

Sealed with printed neckband for your protection

Compare to Orajel™ Antiseptic Rinse for all Mouth Sores*

ORAL SORE

ANTISEPTIC RINSE

TEMPORARY PAIN RELIEF FOR MOUTH SORES

MINT

for mouth sores, including gum irritation from braces or dentures and canker sores

kills germs and bacteria

helps alleviate pain

473 mL (16 FL OZ)